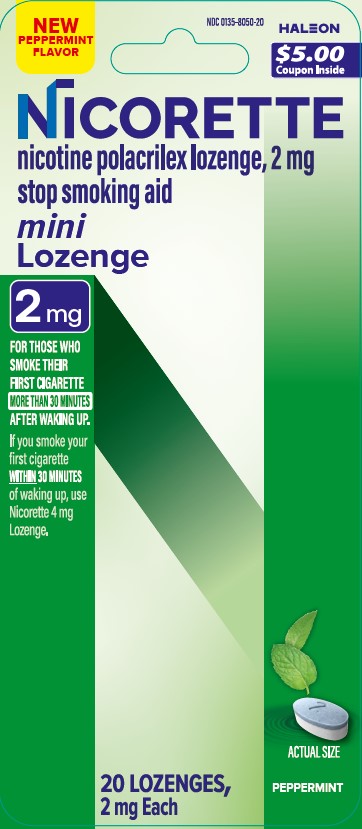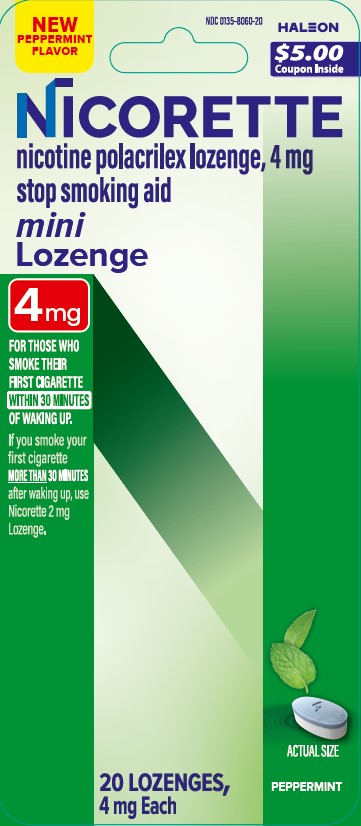 DRUG LABEL: Nicorette
NDC: 0135-8050 | Form: LOZENGE
Manufacturer: Haleon US Holdings LLC
Category: otc | Type: HUMAN OTC DRUG LABEL
Date: 20250731

ACTIVE INGREDIENTS: NICOTINE 2 mg/1 1
INACTIVE INGREDIENTS: ACESULFAME POTASSIUM; ANHYDROUS DIBASIC CALCIUM PHOSPHATE; CROSPOVIDONE, UNSPECIFIED; FD&C BLUE NO. 2 ALUMINUM LAKE; HYPROMELLOSE, UNSPECIFIED; MAGNESIUM STEARATE; MANNITOL; MICROCRYSTALLINE CELLULOSE; SODIUM BICARBONATE; SODIUM CARBONATE; SUCRALOSE; XANTHAN GUM; XYLITOL

Drug Facts

Active ingredient (in each lozenge) – 2 mg

Nicotine polacrilex, 2 mg

Active ingredient (in each lozenge) – 4 mg

Nicotine polacrilex, 4 mg

Purpose

Stop smoking aid

Use

- reduces withdrawal symptoms, including nicotine craving, associated with quitting smoking

Warnings

If you are pregnant or breast-feeding, only use this medicine on the advice of your health care provider.

Smoking can seriously harm your child. Try to stop smoking without using any nicotine replacement medicine. This medicine is believed to be safer than smoking. However, the risks to your child from this medicine are not fully known.

Ask a doctor before use if you have

- heart disease, recent heart attack, or irregular heartbeat. Nicotine can increase your heart rate.
- high blood pressure not controlled with medication. Nicotine can increase your blood pressure.
- stomach ulcer or diabetes
- history of seizures

Ask a doctor or pharmacist before use if you are

- using a non-nicotine stop smoking drug
- taking a prescription medicine for depression or asthma. Your prescription dose may need to be adjusted.

Stop use and ask a doctor if

- mouth problems occur
- persistent indigestion or severe sore throat occurs
- irregular heartbeat or palpitations occur
- you get symptoms of nicotine overdose such as nausea, vomiting, dizziness, diarrhea, weakness and rapid heartbeat
- you have symptoms of an allergic reaction (such as difficulty breathing or rash)

Keep out of reach of children and pets.

Nicotine lozenges may have enough nicotine to make children and pets sick. If you need to remove the lozenge, wrap it in paper and throw away in the trash. In case of overdose, get medical help or contact a Poison Control Center right away.

Directions

- if you are under 18 years of age, ask a doctor before use. No studies have been done to show if this product will work for you.
- before using this product, read the enclosed User’s Guide for complete directions and other important information
- begin using the lozenge on your quit day
- if you smoke your first cigarette within 30 minutes of waking up, use 4 mg nicotine lozenge
- if you smoke your first cigarette more than 30 minutes after waking up, use 2 mg nicotine lozenge according to the following 12 week schedule:

Weeks 1 to 6 | Weeks 7 to 9 | Weeks 10 to 12
1 lozenge every 1 to 2 hours | 1 lozenge every 2 to 4 hours | 1 lozenge every 4 to 8 hours

- nicotine lozenge is a medicine and must be used a certain way to get the best results
- place the lozenge in your mouth and allow the lozenge to slowly dissolve. Minimize swallowing. Do not chew or swallow lozenge.
- you may feel a warm or tingling sensation
- occasionally move the lozenge from one side of your mouth to the other until completely dissolved
- do not eat or drink 15 minutes before using or while the lozenge is in your mouth
- to improve your chances of quitting, use at least 9 lozenges per day for the first 6 weeks
- do not use more than one lozenge at a time or continuously use one lozenge after another since this may cause you hiccups, heartburn, nausea or other side effects
- do not use more than 5 lozenges in 6 hours. Do not use more than 20 lozenges per day.
- it is important to complete treatment. If you feel you need to use the lozenge for a longer period to keep from smoking, talk to your health care provider.

Other information

- store between 20°-25°C (68°-77°F)
- keep the vial tightly closed and protect from light

Inactive ingredients

acesulfame potassium, anhydrous dibasic calcium phosphate, crospovidone, FD&C blue no. 2 aluminum lake, flavors, hypromellose, magnesium stearate, mannitol, microcrystalline cellulose, sodium bicarbonate, sodium carbonate anhydrous, sucralose, xanthan gum, xylitol

Questions or comments?

call toll-free 1-888-569-1743

Additional Information

TO INCREASE YOUR SUCCESS IN QUITTING:

1. You must be motivated to quit
2. Use Enough – Use at least 9 Nicorette mini Lozenges per day during the first six weeks.
3. Use Long Enough – Use Nicorette mini Lozenges for the full 12 weeks.
4. Use with a support program as directed in the enclosed User’s Guide.

Opening Directions:

Squeeze child resistant tabs on each side. Flip up the top of vial. Turn upside down and shake to remove lozenge.

For more information and for a FREE individualized stop smoking program, please visit www.Nicorette.com or see inside for more details.

Flip open for Directions and additional information

Retain this package for complete product information

- not for sale to those under 18 years of age
- proof of age required
- not for sale in vending machines or from any source where proof of age cannot be verified

TAMPER EVIDENT FEATURE: Do not use if clear neckband printed “SEALED FOR SAFETY” is missing or broken. Retain outer carton for full product uses, directions and warnings.

Principal Display Panel – 2 mg

NEW PEPPERMINT FLAVOR

NDC 0135-8050-20

$5.00 Coupon Inside

NICORETTE

nicotine polacrilex lozenge, 2 mg

stop smoking aid

mini

Lozenge

2 mg

FOR THOSE WHO SMOKE THEIR FIRST CIGARETTE MORE THAN 30 MINUTES AFTER WAKING UP.

If you smoke your first cigarette WITHIN 30 MINUTES of waking up, use Nicorette 4 mg Lozenge.

20 LOZENGES, 2 mg Each

ACTUAL SIZE

PEPPERMINT

Principal Display Panel – 4 mg

NEW PEPPERMINT FLAVOR

NDC 0135-8060-20

$5.00 Coupon Inside

NICORETTE

nicotine polacrilex lozenge, 4 mg

stop smoking aid

mini

Lozenge

4 mg

FOR THOSE WHO SMOKE THEIR FIRST CIGARETTE WITHIN 30 MINUTES OF WAKING UP.

If you smoke your first cigarette MORE THAN 30 MINUTES after waking up, use Nicorette 2 mg Lozenge.

20 LOZENGES, 4 mg Each

ACTUAL SIZE

PEPPERMINT